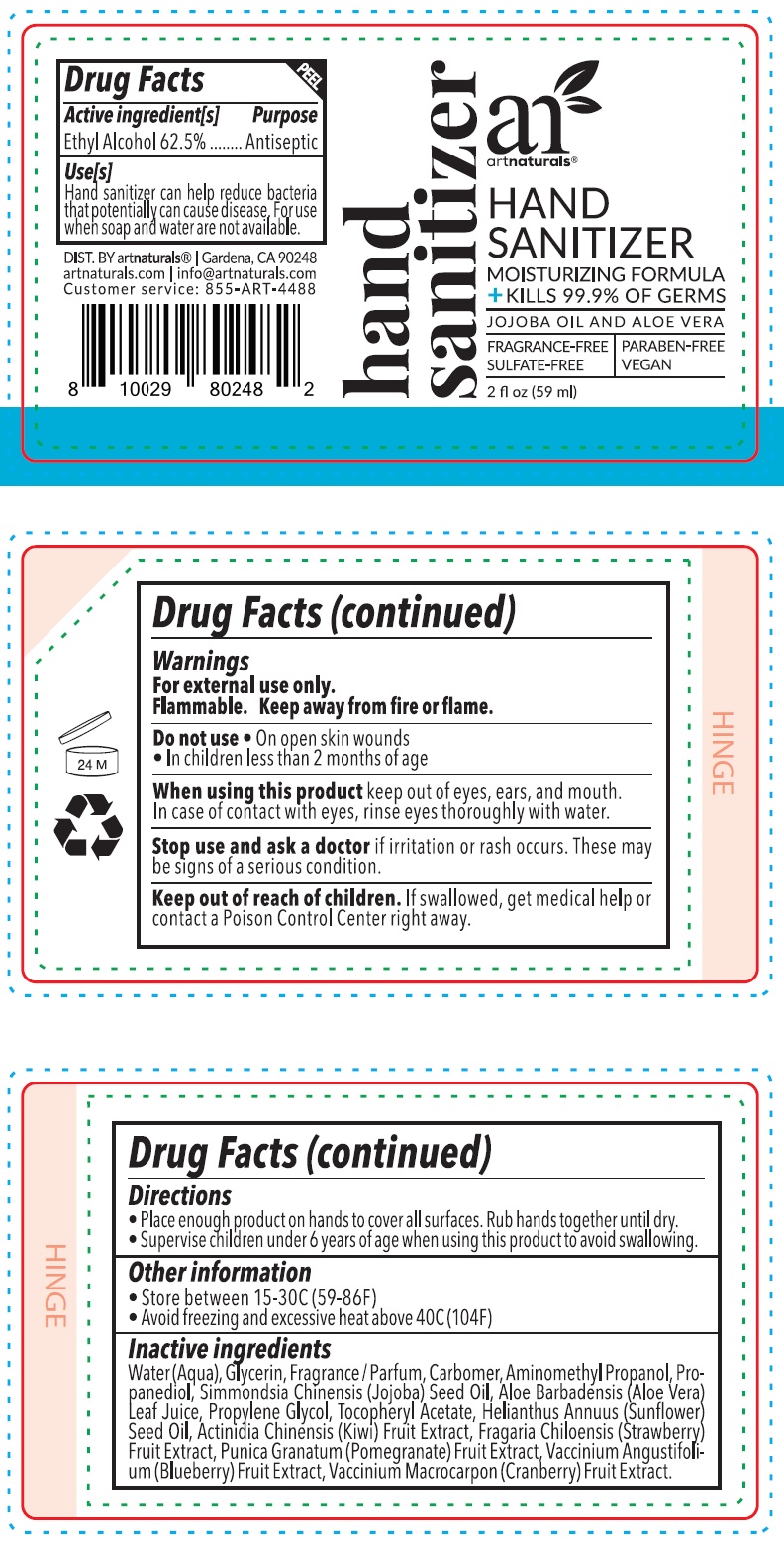 DRUG LABEL: Artnaturals Hand Sanitizer Moisturizing Formula
NDC: 78706-004 | Form: GEL
Manufacturer: Virgin Scent Inc.
Category: otc | Type: HUMAN OTC DRUG LABEL
Date: 20201019

ACTIVE INGREDIENTS: ALCOHOL 0.625 mL/1 mL
INACTIVE INGREDIENTS: WATER; GLYCERIN; CARBOMER HOMOPOLYMER, UNSPECIFIED TYPE; AMINOMETHYLPROPANOL; PROPANEDIOL; JOJOBA OIL; ALOE VERA LEAF; PROPYLENE GLYCOL; .ALPHA.-TOCOPHEROL ACETATE; SUNFLOWER OIL; KIWI FRUIT; BEACH STRAWBERRY; POMEGRANATE; LOWBUSH BLUEBERRY; CRANBERRY

Artnaturals Hand Sanitizer Moisturizing Formula

Active ingredient[s]

Ethyl Alcohol 62.5%

Purpose

Antiseptic

Use[s]

Hand sanitizer can help reduce bacteria that potentially can cause disease. For use when soap and water are not available.

Warnings

For external use only.

Flammable. Keep away from fire or flame.

Do not use

- On open skin wounds
- In children less than 2 months of age

When using this product

keep out of eyes, ears, and mouth. In case of contact with eyes, rinse eyes thoroughly with water.

Stop use and ask a doctor

if irritation or rash occurs. These may be signs of a serious condition.

Keep our of reach of children.

If swallowed, get medical help or contact a Poison Control Center right away.

Directions

- Place enough product on hands to cover all surfaces. Rub hands together until dry.
- Supervise children under 6 years of age when using this product to avoid swallowing.

Other information

- Store between 15-30C (59-86F)
- Avoid freezing and excessive heat above 40C (104F)

Inactive ingredients

Water (Aqua), Glycerin, Fragrance / Parfum, Carbomer, Aminomethyl Propanol, Propanediol, Simmondsia Chinensis (Jojoba) Seed Oil, Aloe Barbadensis (Aloe Vera) Leaf Juice, Propylene Glycol, Tocopheryl Acetate, Helianthus Annuus (Sunflower) Seed Oil, Actinidia Chinensis (Kiwi) Fruit Extract, Fragaria Chiloensis (Strawberry) Fruit Extract, Punica Granatum (Pomegranate) Fruit Extract, Vaccinium Angustifolium (Blueberry) Fruit Extract, Vaccinium Macrocarpon (Cranberry) Fruit Extract.